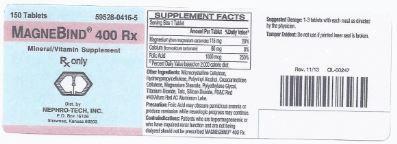 DRUG LABEL: MagneBind 400 Rx
NDC: 59528-0416 | Form: TABLET, FILM COATED
Manufacturer: Nephro-Tech, Inc.
Category: prescription | Type: HUMAN PRESCRIPTION DRUG LABEL
Date: 20140204

ACTIVE INGREDIENTS: MAGNESIUM CARBONATE 115 mg/1 1; CALCIUM CARBONATE 80 mg/1 1; FOLIC ACID 1 mg/1 1
INACTIVE INGREDIENTS: CELLULOSE, MICROCRYSTALLINE; HYDROXYPROPYL CELLULOSE; POLYVINYL ALCOHOL; CROSCARMELLOSE SODIUM; MAGNESIUM STEARATE; POLYETHYLENE GLYCOL 200; TITANIUM DIOXIDE; TALC; SILICON DIOXIDE; FD&C RED NO. 40

MagneBind 400 Rx
magnesium carbonate, calcium carbonate, folic acid tablet, coated

Description

MagneBind 400 Rx is a prescription folic acid supplement with additional nutrients for kidney diaylsis patients. MagneBind 400 Rx is a pink, film-coated, oval shaped tablet.

Suggested Dosage

1-3 tablets with each meal as directed by the physician.

Contraindications

Patients who are hypermagnesemic or who have impaired renal function and are not being dialyzed should not be prescribed MagneBind 400 Rx.

Package Label/Principal Display Panel

59528-0416-05

Rx Only

MagneBind 400 Rx

Mineral/Vitamin Supplement

150 tablets